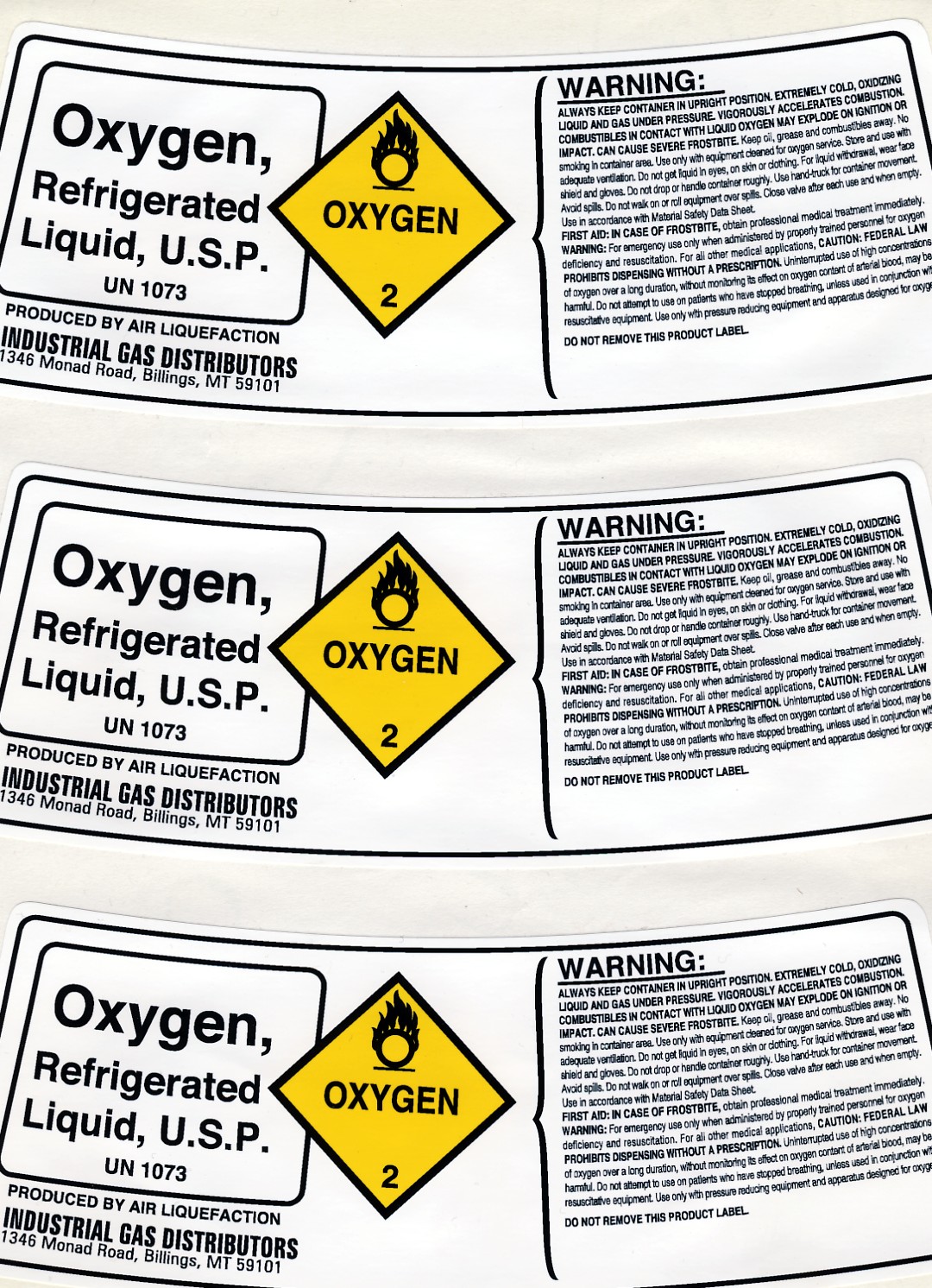 DRUG LABEL: Oxygen
NDC: 11331-001 | Form: GAS
Manufacturer: American Welding & Gas
Category: prescription | Type: HUMAN PRESCRIPTION DRUG LABEL
Date: 20091106

ACTIVE INGREDIENTS: Oxygen 99 L/100 L

Liquid Oxygen Label

PACKAGE LABEL

Oxygen, Refrigerated Liquid, U.S.P. UN 1073

WARNING:

ALWAYS KEEP CONTAINER IN UPRIGHT POSITION. EXTREMELY COLD, OXIDIZING LIQUID AND GOS UNDER PRESSURE. VIGOROUSLY ACCELERATES COMBUSTION. COMBUSTIBLES IN CONTACT WITH LIQUID OXYGEN MAY EXPLODE ON IGNITION OR IMPACT. CAN CAUSE SEVERE FROSTBITE. Keep oil, grease and combustibles away. No smoking in container area. Use only equipment cleaned for oxygen service. Store and use with adequate ventilation. Do not get liquid in eyes, on skin or clothing. For liquid withdrawal, wear face shield and gloves. Do not drop or handle container roughly. Use hand-truck for container movement. Avoid spills. Do not walk on or roll equipment over spills. Close valve after each use and when empty. Use in accordance with Material Safety Date Sheet.

FIRST AID: IN CASE OF FROSTBITE, obtain professional medical treatment immediately.

WARNING: For emergency use only when administered by properly trained personnel for oxygen deficiency and resuscitation. For all other medical applications, CAUTION: FEDERAL LAW PROHIBITS DISPENSING WITHOUT A PRESCRIPTION. Uninterrupted use of high concentrations of oxygen over a long duration, without monitoring its effect on oxygen content of arterial blood, may be harmful. Do not attempt to use on patients who have stopped breathing, unless used in conjunction with resuscitative equipment. Use only with pressure reducing equipment and apparatus designed for oxygen.

DO NOT REMOVE THIS PRODUCT LABEL